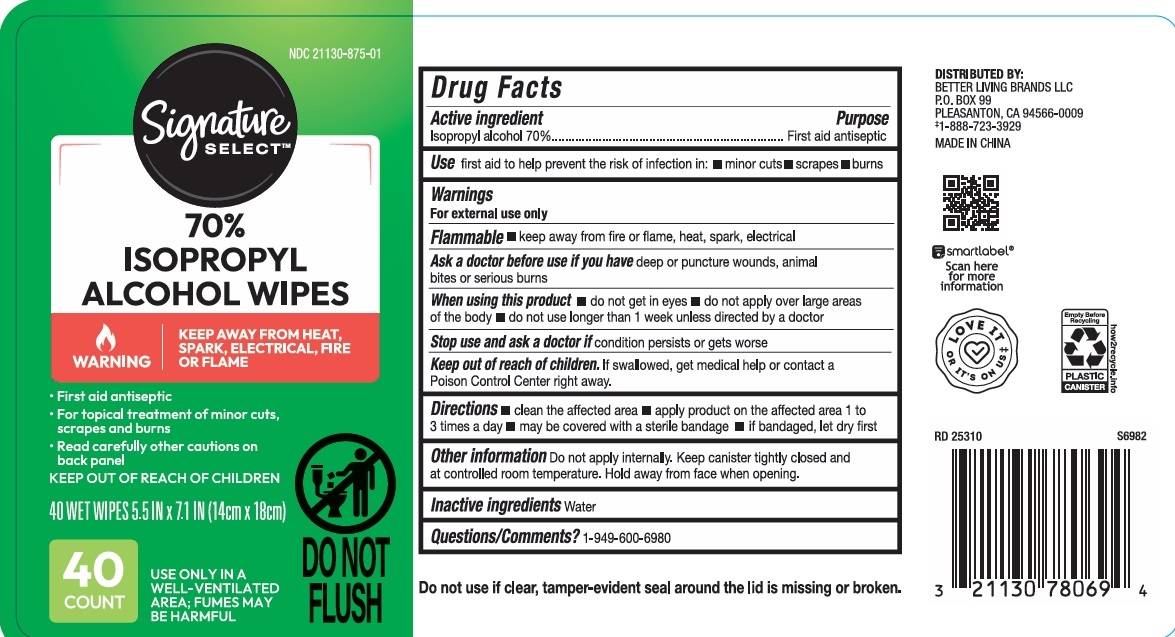 DRUG LABEL: Signature Select Isopropyl Alcohol Wipes (40 count)
NDC: 21130-875 | Form: CLOTH
Manufacturer: Better Living Brands LLC
Category: otc | Type: HUMAN OTC DRUG LABEL
Date: 20251217

ACTIVE INGREDIENTS: ISOPROPYL ALCOHOL 70 g/100 g
INACTIVE INGREDIENTS: WATER

Signature Select Isopropyl Alcohol Wipes (40 count)

Active ingredient

Isopropyl Alcohol 70%

Purpose

first aid antiseptic

Use

First aid to help prevent the risk of infection in:

- minor cuts
- scrapes
- burns

Warnings

For external use only

Flammable.

- Keep away from fire and flame, heat, spark, electrical

When using this product

- do not get in eyes
- do not apply over large areas of the body
- do not use longer than 1 week unless directed by a doctor

Ask a doctor before use if you have deep or puncture wounds, animal bites or serious burns.

Stop use and ask a doctor if condition persistss or gets worse

Other Information

Do not apply internally. Keep canister tightly closed and at controlled room temperature. Hold away from face when opening.

Keep out of reach of children.

- If swallowed, get medical help or contact a Poison Control Center right away.

Directions

- clean the affected area
- apply product on the affected area 1 to 3 times a day
- may be covered with a terile bandage
- if bandaged, let dry first

Inactive ingredients

Water

1-888-723-3929